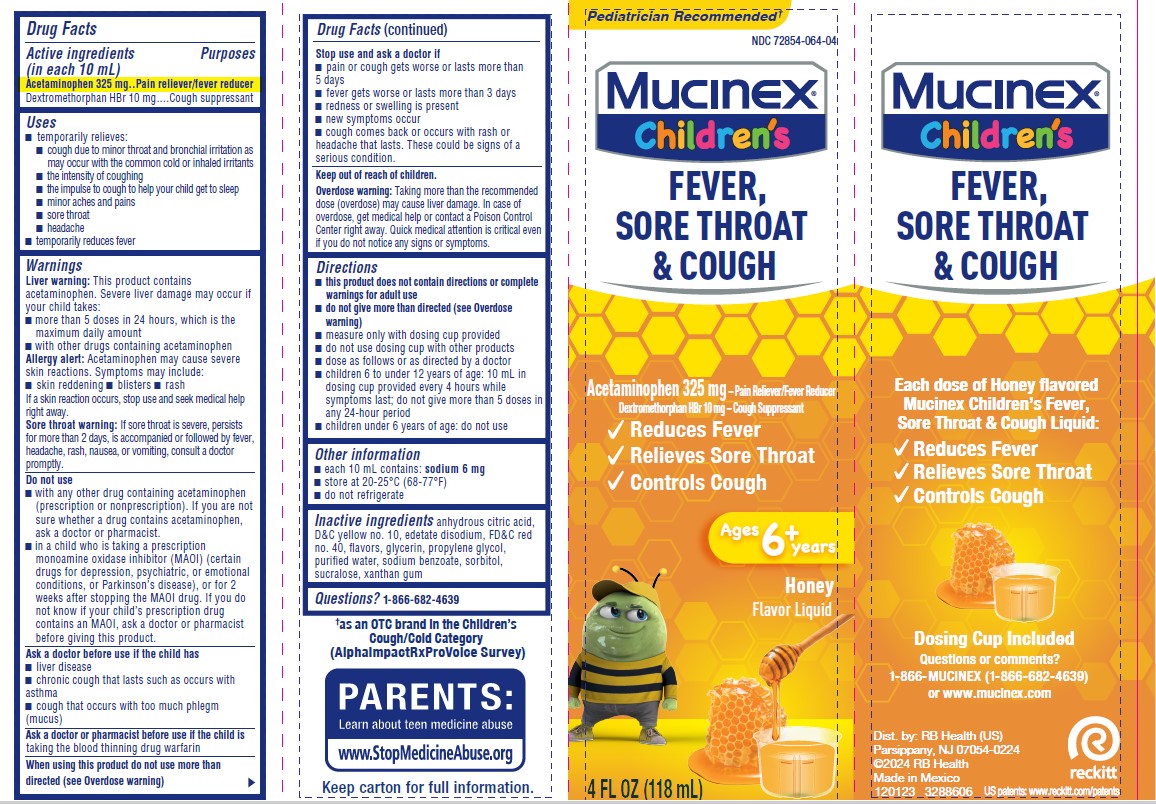 DRUG LABEL: Mucinex Childrens Fever Sore Throat and Cough
NDC: 72854-064 | Form: SOLUTION
Manufacturer: RB Health (US) LLC
Category: otc | Type: HUMAN OTC DRUG LABEL
Date: 20240403

ACTIVE INGREDIENTS: ACETAMINOPHEN 325 mg/10 mL; DEXTROMETHORPHAN HYDROBROMIDE 10 mg/10 mL
INACTIVE INGREDIENTS: PROPYLENE GLYCOL; ANHYDROUS CITRIC ACID; WATER; GLYCERIN; D&C YELLOW NO. 10; XANTHAN GUM; FD&C RED NO. 40; SORBITOL; SUCRALOSE; EDETATE DISODIUM; SODIUM BENZOATE

Mucinex Children's Fever, Sore Throat & Cough

Active ingredients / Purpose (in each 10 mL)

Acetaminophen 325 mg..Pain reliever/fever reducer
Dextromethorphan HBr 10 mg....Cough suppressant

PURPOSE

Acetaminophen 325 mg..Pain reliever/fever reducer
Dextromethorphan HBr 10 mg....Cough suppressant

Uses

■ temporarily relieves:
■ cough due to minor throat and bronchial irritation as
may occur with the common cold or inhaled irritants
■ the intensity of coughing
■ the impulse to cough to help your child get to sleep
■ minor aches and pains
■ sore throat
■ headache
■ temporarily reduces fever

Warnings
Liver warning: This product contains
acetaminophen. Severe liver damage may occur if
your child takes:
■ more than 5 doses in 24 hours, which is the
maximum daily amount
■ with other drugs containing acetaminophen
Allergy alert: Acetaminophen may cause severe
skin reactions. Symptoms may include:
■ skin reddening

■ blisters

■ rash

If a skin reaction occurs, stop use and seek medical help
right away.

Sore throat warning: If sore throat is severe, persists
for more than 2 days, is accompanied or followed by fever,
headache, rash, nausea, or vomiting, consult a doctor
promptly.

Do not use
■ with any other drug containing acetaminophen
(prescription or nonprescription). If you are not
sure whether a drug contains acetaminophen,
ask a doctor or pharmacist.
■ in a child who is taking a prescription
monoamine oxidase inhibitor (MAOI) (certain
drugs for depression, psychiatric, or emotional
conditions, or Parkinson’s disease), or for 2
weeks after stopping the MAOI drug. If you do
not know if your child’s prescription drug
contains an MAOI, ask a doctor or pharmacist
before giving this product.

Ask a doctor before use if the child has
■ liver disease
■ chronic cough that lasts such as occurs with
asthma
■ cough that occurs with too much phlegm
(mucus)

Ask a doctor or pharmacist before use if the child is
taking the blood thinning drug warfarin

Stop use and ask a doctor if
■ pain or cough gets worse or lasts more than
5 days
■ fever gets worse or lasts more than 3 days
■ redness or swelling is present
■ new symptoms occur
■ cough comes back or occurs with rash or
headache that lasts. These could be signs of a
serious condition.

Keep out of reach of children.

Overdose warning: Taking more than the recommended
dose (overdose) may cause liver damage. In case of
overdose, get medical help or contact a Poison Control
Center right away. Quick medical attention is critical even
if you do not notice any signs or symptoms

Directions

■ this product does not contain directions or complete
warnings for adult use
■ do not give more than directed (see Overdose
warning)
■ measure only with dosing cup provided
■ do not use dosing cup with other products
■ dose as follows or as directed by a doctor
■ children 6 to under 12 years of age: 10 mL in
dosing cup provided every 4 hours while
symptoms last; do not give more than 5 doses in
any 24-hour period
■ children under 6 years of age: do not use

Other information
■ each 10 mL contains: sodium 6 mg
■ store at 20-25°C (68-77°F)
■ do not refrigerate

Inactive ingredients: anhydrous citric acid,
D&C yellow no. 10, edetate disodium, FD&C red
no. 40, flavors, glycerin, propylene glycol,
purified water, sodium benzoate, sorbitol,
sucralose, xanthan gum

Questions? 1-866-682-4639

PACKAGE LABEL

NDC 72854-064

Children's
Mucinex®

Honey
Flavor Liquid

4 FL OZ
(118 mL)